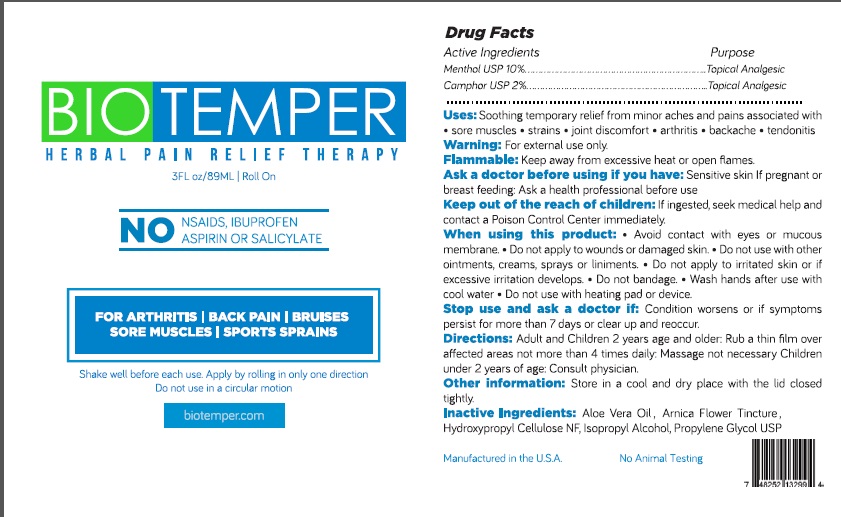 DRUG LABEL: Biotemper
NDC: 70744-516 | Form: LIQUID
Manufacturer: Biotemper
Category: otc | Type: HUMAN OTC DRUG LABEL
Date: 20160630

ACTIVE INGREDIENTS: MENTHOL 10 g/100 mL; CAMPHOR (SYNTHETIC) 2 g/100 mL
INACTIVE INGREDIENTS: ALOE VERA LEAF; ARNICA MONTANA FLOWER; HYDROXYPROPYL CELLULOSE (TYPE E); ISOPROPYL ALCOHOL; PROPYLENE GLYCOL

Biotemper - Herbal Pain Relief Therapy

Active Ingredients

Menthol USP 10%.

Camphor USP 2%

Purpose

Topical Analgesic

KEEP OUT OF REACH OF CHILDREN

Keep out of the reach of children: If ingested, seek medical help and contact a Poison Control Center immediately.

INDICATIONS AND USAGE

Uses : Soothing temporary relief from minor aches and pains associated with • sore muscles • strains • joint discomfort • arthritis • backache • tendonitis

WARNINGS

Warning: For external use only.

Flammable: Keep away from excessive heat or open flames.

Ask a doctor before using if you have: Sensitive skin If pregnant or breast feeding: Ask a health professional before use.

When using this product: • Avoid contact with eyes or mucous membrane. • Do not apply to wounds or damaged skin. • Do not use with other ointments, creams, sprays or liniments. • Do not apply to irritated skin or if excessive irritation develops. • Do not bandage. • Wash hands after use with cool water • Do not use with heating pad or device.
Stop use and ask a doctor if: Condition worsens or if symptoms persist for more than 7 days or clear up and reoccur.

DOSAGE AND ADMINISTRATION

Directions: Adult and Children 2 years age and older: Rub a thin film over affected areas not more than 4 times daily: Massage not necessary Children under 2 years of age: Consult physician.

INACTIVE INGREDIENT

Inactive Ingredients: Aloe Vera Oil, Arnica Flower Tincture, Hydroxypropyl Cellulose NF, Isopropyl Alcohol, Propylene Glycol USP

Other information: Store in a cool and dry place with the lid closed tightly.

NO NSAIDS, IBUPROFEN, ASPIRIN OR SALICYLATE

FOR ARTHRITIS/BACK PAIN/ BRUISES/SORE MUSCLES/ SPORTS SPRAINS

Shake well before each use. Apply by rolling in only one direction.

Do not use in a circular motion